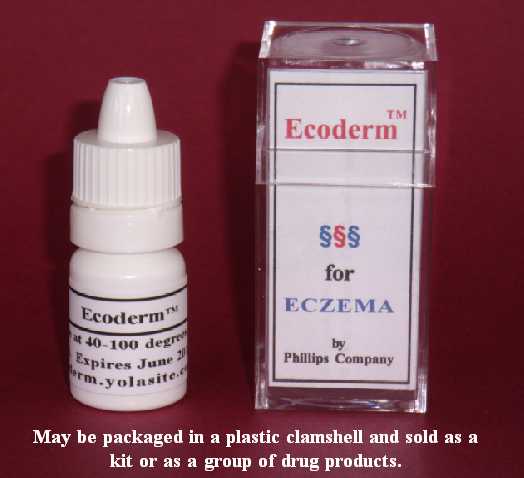 DRUG LABEL: Ecoderm
NDC: 43074-113 | Form: LOTION
Manufacturer: Phillips Company
Category: otc | Type: HUMAN OTC DRUG LABEL
Date: 20110116

ACTIVE INGREDIENTS: OATMEAL 0.001 mL/1 mL
INACTIVE INGREDIENTS: dimethyl sulfoxide; ascorbic acid; dipropylene glycol; water; sorbic acid; magnesium stearate; stearic acid; sodium dodecylbenzenesulfonate

DRUG FACTS

DRUG FACTS

Active Ingredient Purpose
Colloidal Oatmeal (0.1%) Skin Protectant
Aka Avena sativa (0.1%) Skin Protectant
________________________________________
Uses
n Temporarily protects and helps relieve minor skin irritation and itching due to eczema.
________________________________________
Warnings
n For external use only
n Keep away from children
n Avoid contact with eyes
n May be harmful if swallowed or inhaled
________________________________________
Ask a physician
n If symptoms last for more than 7 days or clear up and recur within a few days.
n If the conditions do not improve.
n Before use on children under 2 years.
n Before use if you are allergic to any ingredients listed on this label.
________________________________________
Directions
Apply to affected skin area and rub gently. Repeat the process as needed.
________________________________________
Other information
This is an OTC skin protectant drug product for human use. Store at 40 to 100 degrees F. Net contents: 3 mL (dropper bottle). This product contains no alcohol; no animal products.
________________________________________
Inactive ingredients
Water, dimethyl sulfoxide, dipropylene glycol, ascorbic acid, sorbic acid, magnesium stearate, stearic acid.
________________________________________
Questions and Side effects
Use of this product results in no known side effects when used according to directions. Phillips Company, 311 Chickasaw Street, Millerton, OK USA 74750; Tel. 580-746-2430
Email address: hp@valliant.net

ACTIVE INGREDIENTS

Colloidal Oatmeal (0.1%) Skin Protectant
Aka Avena sativa (0.1%) Skin Protectant

ASK DOCTOR

Ask a doctor
n If symptoms last for more than 7 days or clear up and recur within a few days.
n If the conditions do not improve.
n Before use on children under 2 years.
n Before use if you are allergic to any ingredients listed on this label.

DO NOT USE

n Avoid contact with eyes
n May be harmful if swallowed or inhaled

CHILDREN

Keep away from children
Avoid contact with eyes
May be harmful if swallowed or inhaled

PURPOSE

n Temporarily protects and helps relieve minor skin irritation and itching due to eczema.

STOP USE

n For external use only
n Keep away from children
n Avoid contact with eyes
n May be harmful if swallowed or inhaled
________________________________________
Ask a physician
n If symptoms last for more than 7 days or clear up and recur within a few days.
n If the conditions do not improve.
n Before use on children under 2 years.
n Before use if you are allergic to any ingredients listed on this label.

WHEN USING

Apply to affected skin area and rub gently. Repeat the process as needed.
Store at 40 to 100 degrees F.
n Temporarily protects and helps relieve minor skin irritation and itching due to eczema.
n For external use only
n Keep away from children
n Avoid contact with eyes
n May be harmful if swallowed or inhaled
Ask a physician If symptoms last for more than 7 days or clear up and recur within a few days.

WARNINGS

n For external use only
n Keep away from children
n Avoid contact with eyes
n May be harmful if swallowed or inhaled

DOSAGE & ADMINISTRATION

Apply to affected skin area and rub gently. Repeat the process as needed.

USE

Uses
n Temporarily protects and helps relieve minor skin irritation and itching due to eczema.
Directions
Apply to affected skin area and rub gently. Repeat the process as needed.

INACTIVE INGREDIENTS

Water, dimethyl sulfoxide, dipropylene glycol, ascorbic acid, sorbic acid, magnesium stearate, stearic acid.

Image of product